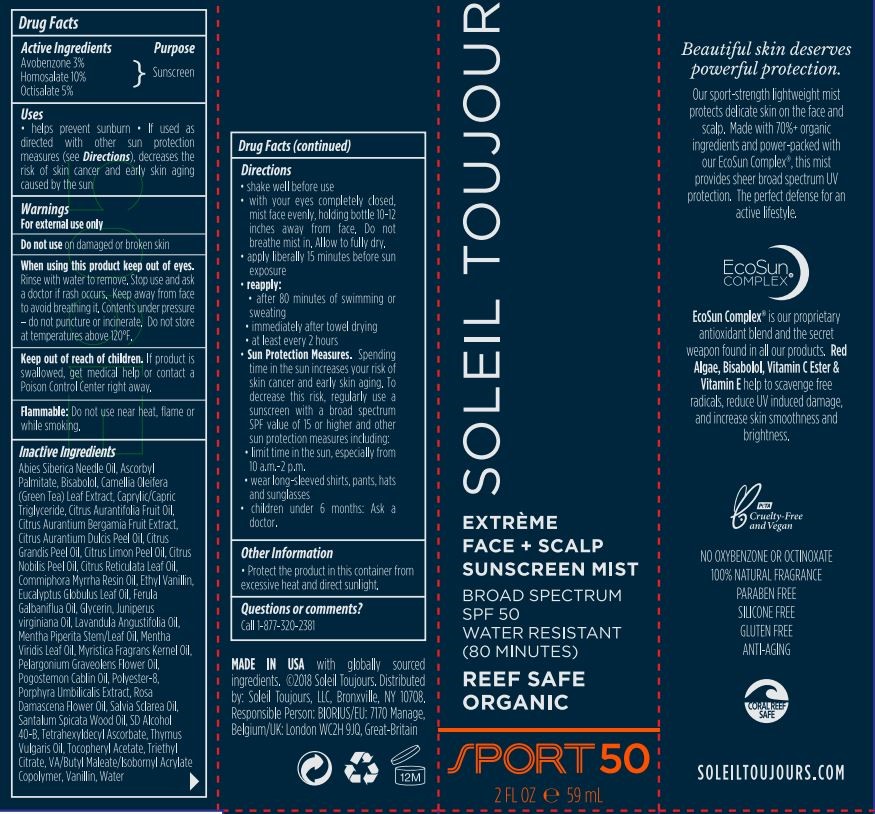 DRUG LABEL: Soleil Toujours
NDC: 13630-0200 | Form: SPRAY
Manufacturer: Prime Packaging Inc.
Category: otc | Type: HUMAN OTC DRUG LABEL
Date: 20211129

ACTIVE INGREDIENTS: AVOBENZONE 25.2 mg/1 mL; HOMOSALATE 83.9 mg/1 mL; OCTISALATE 42 mg/1 mL
INACTIVE INGREDIENTS: ASCORBYL PALMITATE; TOCOPHEROL; GLYCERIN; GREEN TEA LEAF; .ALPHA.-TOCOPHEROL ACETATE; ALCOHOL; POLYESTER-8 (1400 MW, CYANODIPHENYLPROPENOYL CAPPED); TETRAHEXYLDECYL ASCORBATE; PORPHYRA UMBILICALIS; WATER; DIBUTYL MALEATE; LEVOMENOL; VINYL ACETATE; ISOBORNYL ACRYLATE

Soleil Toujours Face and Scalp Sunscreen Mist Broad Spectrum SPF 50

Active Ingredients

Avobenzone 3%

Homosalate 10%

Octisalate 5%

Purpose

Sunscreen

Uses

- helps prevent sunburn
- if used as directed with other sun protection measures (see Directions), decreases the risk of skin cancer and early skin aging caused by the sun

Warnings

For external use only.

Do not use on damaged or broken skin.

When using this product keep out of eyes. Rinse with water to remove. Keep away from face to avoid breathing it. Contents under pressure- do not puncture or incinerate it. Do not store at temperatures above 120ºF.

Keep out of reach of children. If product is swallowed, get medical help or contact a Poison Control Center right away.

Flammable: Contents under pressure. Do not puncture or incinerate. Do no store at temperatures above 120°F. Do not use in the presence of a flame or spark, or while smoking.

INACTIVE INGREDIENT

Abies Siberica Needle Oil, Ascorbyl Palmitate, Bisabolol, Camellia Oleifera (Green Tea) Leaf Extract, Caprylic/Capric Triglyceride, Citrus Aurantifolia Fruit Oil, Citrus Aurantium Bergamia Fruit Extract, Citrus Aurantium Dulcis Peel Oil, Citrus Grandis Peel Oil, Citrus Limon Peel Oil, Citrus Nobilis Peel Oil, Citrus Reticulata Leaf Oil, Commiphora Myrrha Resin Oil, Ethyl Vanillin, Eucalyptus Globulus Leaf Oil, Ferula Galbaniflua Oil, Glycerin, Juniperus virginiana Oil, Lavandula Angustifolia Oil, Mentha Piperita Stem/Leaf Oil, Mentha Viridis Leaf Oil, Myristica Fragrans Kernel Oil, Pelargonium Graveolens Flower Oil, Pogostemon Cablin Oil, Polyester-8, Porphyra Umbilicalis Extract, Rosa Damascena Flower Oil, Salvia Sclarea Oil, Santalum Spicata Wood Oil, SD Alcohol 40-B, Tetrahexyldecyl Ascorbate, Thymus Vulgaris Oil, Tocopheryl Acetate, Triethyl Citrate, VA/Butyl Maleate/Isobornyl Acrylate Copolymer, Vanillin, Water

Directions

- Shake well before use
- with your eyes completely closed, mist face evenly, holding bottle 10-12 inches away from face. Do not breath mist in,Allow to fully dry.
- apply liberally 15 minutues before sun exposure
- reapply:
- after 80 minutes of swimming or sweating
- immediately after towel drying
- at least every 2 hours
- Sun Protection Measures. Spending time in the sun increases your risk of skin cancer and early skin aging. To decrease this risk, regularly use a sunscreen with a broad spectrum SPF of 15 or higher and other sun protection measures including:
- limit time in the sun, especially from 10 a. m. - 2 p. m.
- wear long-sleeve shirts, pants, hats, and sunglasses
- children under 6 months: Ask a doctor

Other Information

- protect this product from excessive heat and direct sun

Question or comments?

Call 1-877-320-2381